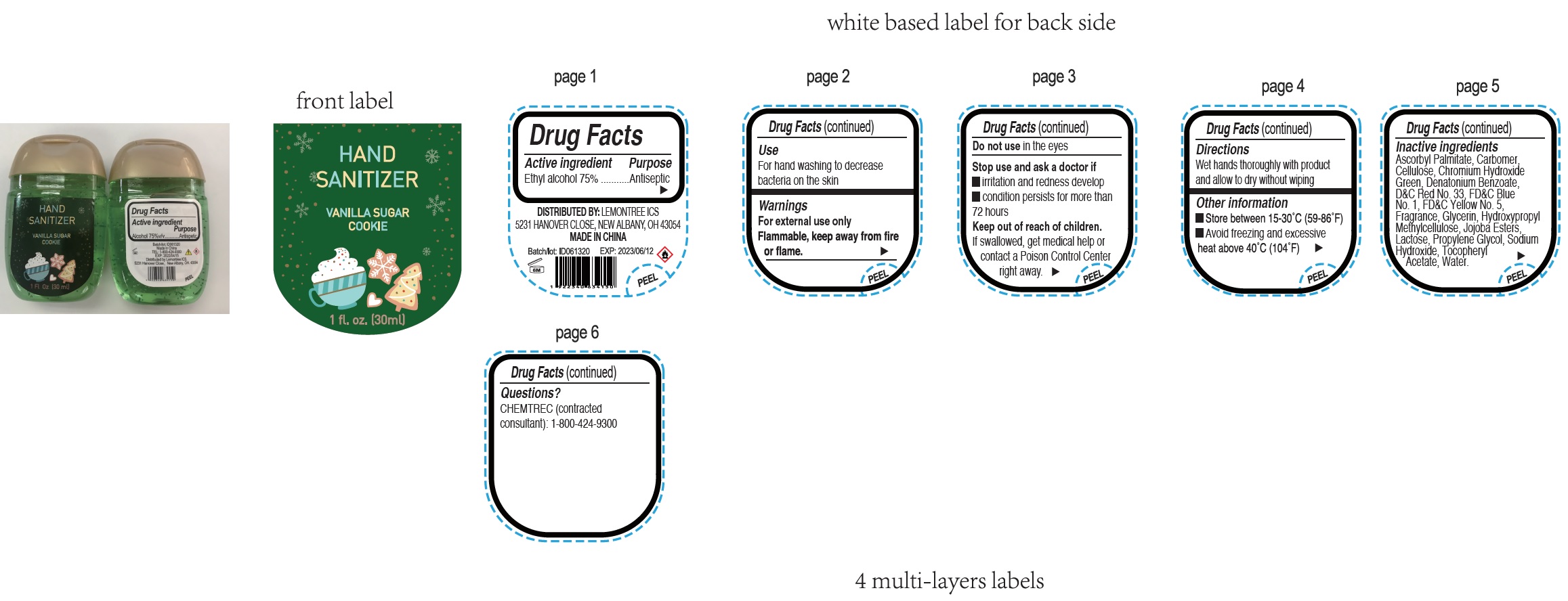 DRUG LABEL: Hand Sanitizer Vanilla Sugar Cookie
NDC: 79834-106 | Form: GEL
Manufacturer: Lemontree ICS
Category: otc | Type: HUMAN OTC DRUG LABEL
Date: 20200810

ACTIVE INGREDIENTS: ALCOHOL 0.75 mL/1 mL
INACTIVE INGREDIENTS: ASCORBYL PALMITATE; CARBOMER HOMOPOLYMER, UNSPECIFIED TYPE; POWDERED CELLULOSE; CHROMIUM HYDROXIDE GREEN; DENATONIUM BENZOATE; D&C RED NO. 33; FD&C BLUE NO. 1; FD&C YELLOW NO. 5; GLYCERIN; HYPROMELLOSE, UNSPECIFIED; LACTOSE, UNSPECIFIED FORM; PROPYLENE GLYCOL; SODIUM HYDROXIDE; .ALPHA.-TOCOPHEROL ACETATE; WATER

Hand Sanitizer, Vanilla Sugar Cookie

Active ingredient

Ethyl alcohol 75%

Purpose

Antiseptic

Use

For hand washing to decrease bacteria on the skin

Warnings

For external use only

Flammable, keep away from fire or flame

Do not use

in the eyes

Stop use and ask a doctor if

- irritation and redness develop
- condition persists for more than 72 hours

Keep out of reach of children.

If swallowed, get medical help or contact a Poison Control Center right away.

Directions

Wet hands thoroughly with product and allow to dry without wiping

Other information

- Store between 15-30°C (59-86°F)
- Avoid freezing and excessive heat above 40°C (104°F)

Inactive ingredients

Ascorbyl Palmitate, Carbomer, Cellulose, Chromium Hydroxide Green, Denatonium Benzoate, Green, Denatonium Benzoate, D&C Red No. 33, FD&C Blue No. 1, FD&C Yellow No. 5, Fragrance, Glycerin, Hydroxypropyl Methylcellulose, Jojoba Esters, Lactose, Propylene Glycol, Sodium Hydroxide, Tocopheryl Acetate, Water.